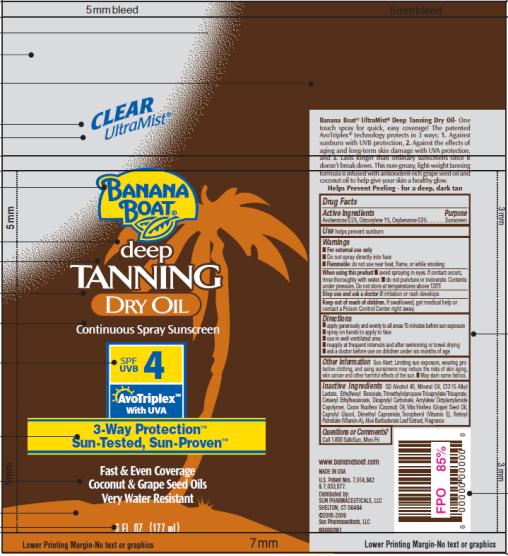 DRUG LABEL: Banana Boat Deep Tanning Dry SPF 4
NDC: 17630-2019 | Form: OIL
Manufacturer: Accra-Pac, Inc.
Category: otc | Type: HUMAN OTC DRUG LABEL
Date: 20100404

ACTIVE INGREDIENTS: AVOBENZONE 0.005 mL/1 mL; OCTOCRYLENE 0.01 mL/1 mL; OXYBENZONE 0.005 mL/1 mL
INACTIVE INGREDIENTS: MINERAL OIL; DICAPRYLYL CARBONATE; GRAPE SEED OIL; COCONUT OIL; CAPRYLYL GLYCOL; ALPHA-TOCOPHEROL; VITAMIN A PALMITATE; ALOE VERA LEAF

Banana Boat Deep Tanning Dry Oil SPF 4

Drug Facts

Active Ingredients

Avobenzone 0.005mL / 1mL

Octocrylene 0.01mL / 1mL

Oxybenzone 0.005mL / 1mL

Purpose

Sunscreen

Use

helps prevent sunburn

Warnings

- For external use only
- Do not spray directly into face
- Flammable: do not use near heat, flame, or while smoking

When using this product

- avoid spraying in eyes. If contact occurs, rinse thoroughly with water.
- do not puncture or incinerate. Contents under pressure. Do not store at temperatures above 120°F.

Stop use and ask a doctor if

irritation or rash develops

Keep out of reach of children.

If swallowed, get medical help or contact a Poison Control Center right away.

Directions

- apply generously and evenly to all areas 15 minutes before sun exposure
- spray on hands to apply to face
- use in well-ventilated area
- reapply at frequent intervals and after swimming or towel drying
- ask a doctor before use on children under six months of age

Other Information

Sun Alert: Limiting sun exposure, wearing protective clothing, and using sunscreens may reduce the risks of skin aging, skin cancer and other harmful effects of the sun.

- May stain some fabrics.

Inactive Ingredients

SD Alcohol 40, Mineral Oil, C12-15 Alkyl Lactate, Ethylhexyl Benzoate, Trimethylolpropane Tricaprylate/ Tricaprate, Cetearyl Ethylhexanoate, Dicaprylyl Carbonate, Acrylates/ Octylacrylamide Copolymer, Cocos Nucifera (Coconut) Oil, Vitis Vinifera (Grape) Seed Oil, Caprylyl Glycol, Dimethyl Capramide, Tocopherol (Vitamin E), Retinyl Palmitate (Vitamin A), Aloe Barbadensis Leaf Extract, Fragrance

Questions or Comments?

Call 1-800 SafeSun, Mon-Fri

MADE IN USA
Distributed by:
SUN PHARMACEUTICALS, LLC
SHELTON, CT 06484

PRINCIPAL DISPLAY PANEL

CLEAR
UltraMist®
BANANA
BOAT®
deep
TANNING
DRY OIL
Continuous Spray Sunscreen
SPF/UVB 4
AvoTriplex TM
With UVA
3-Way Protection TM
Sun-Tested, Sun-Proven TM
Fast & Even Coverate
Coconut & Grape Seed Oils
Very Water Resistant
6 FL. OZ. (177 mL)